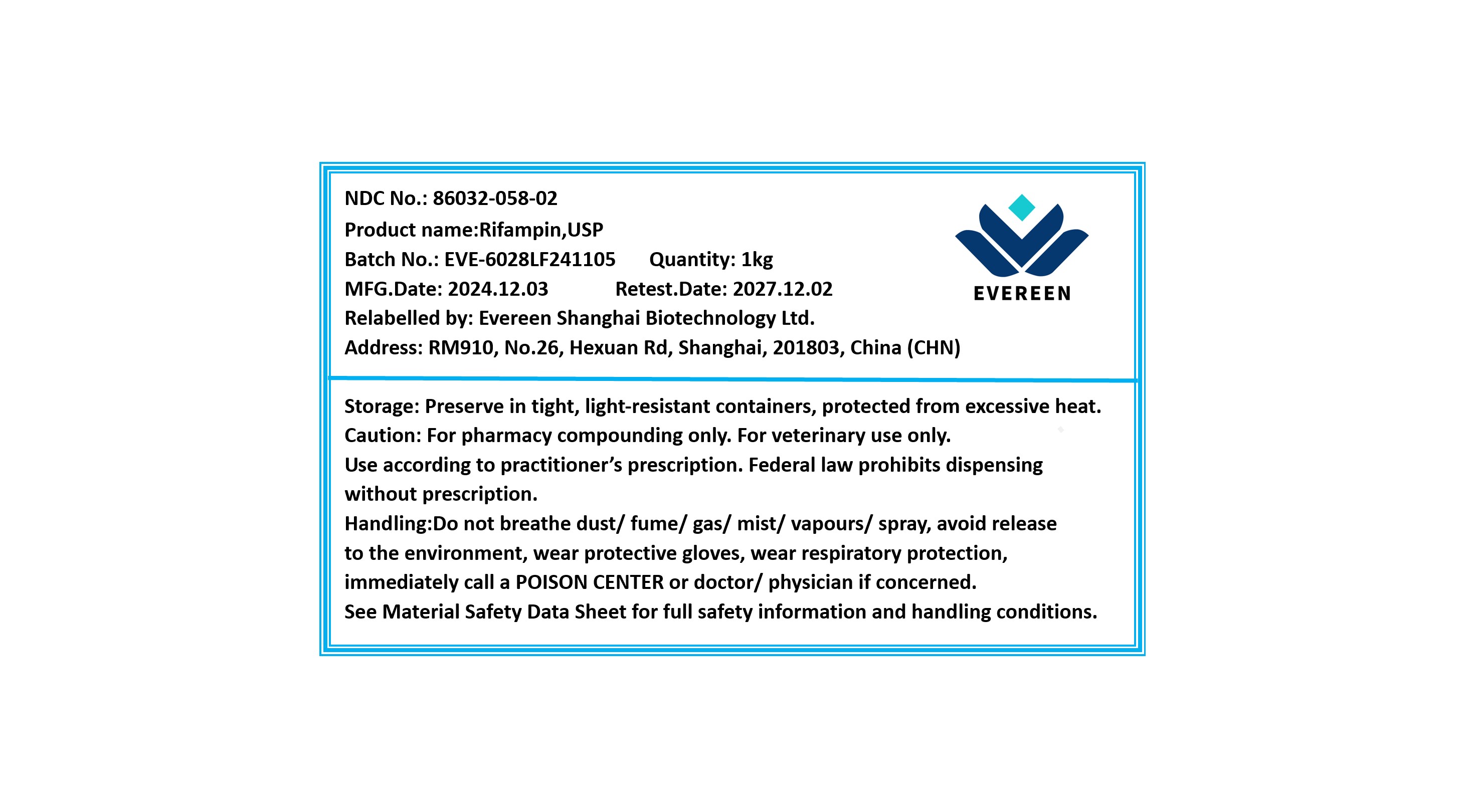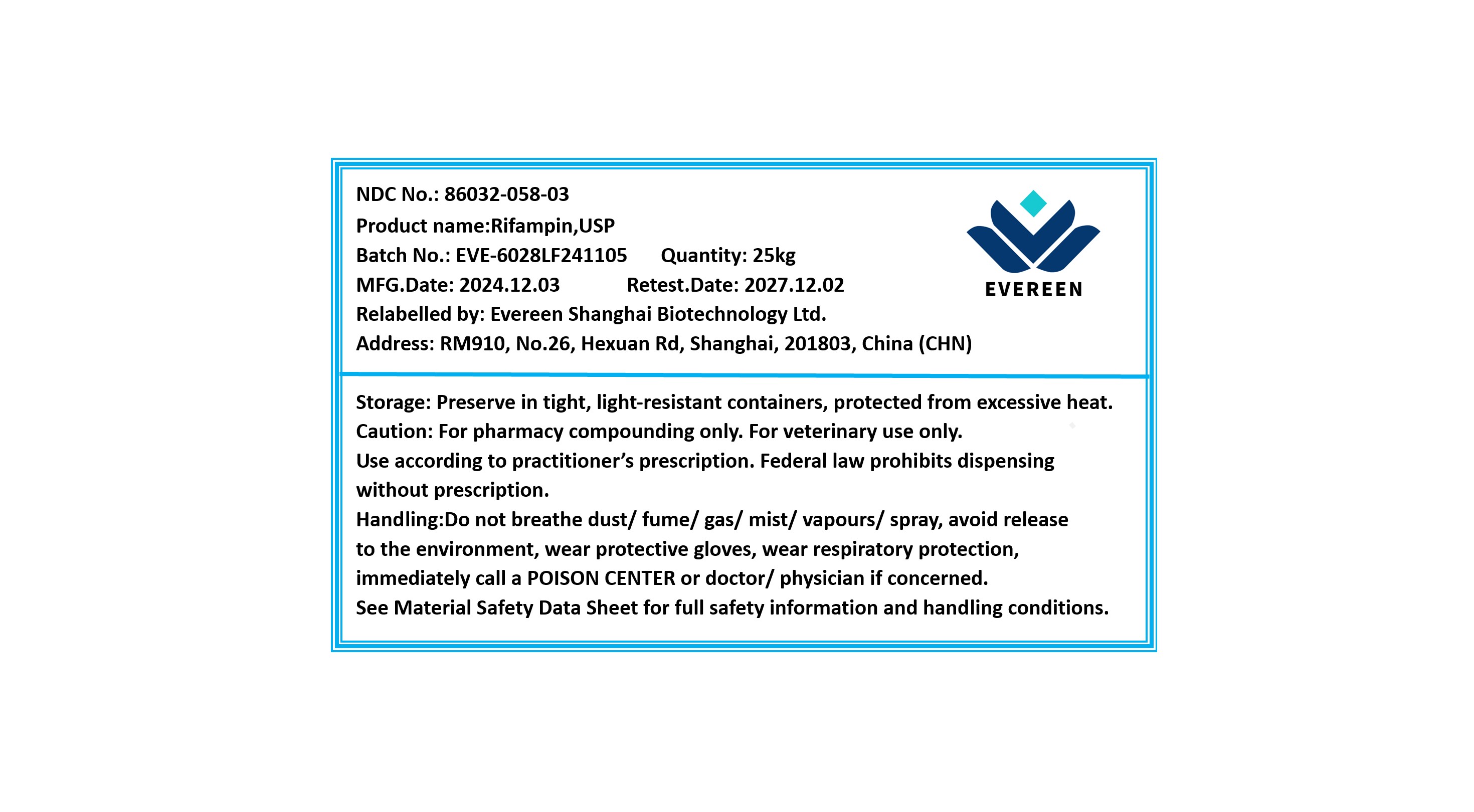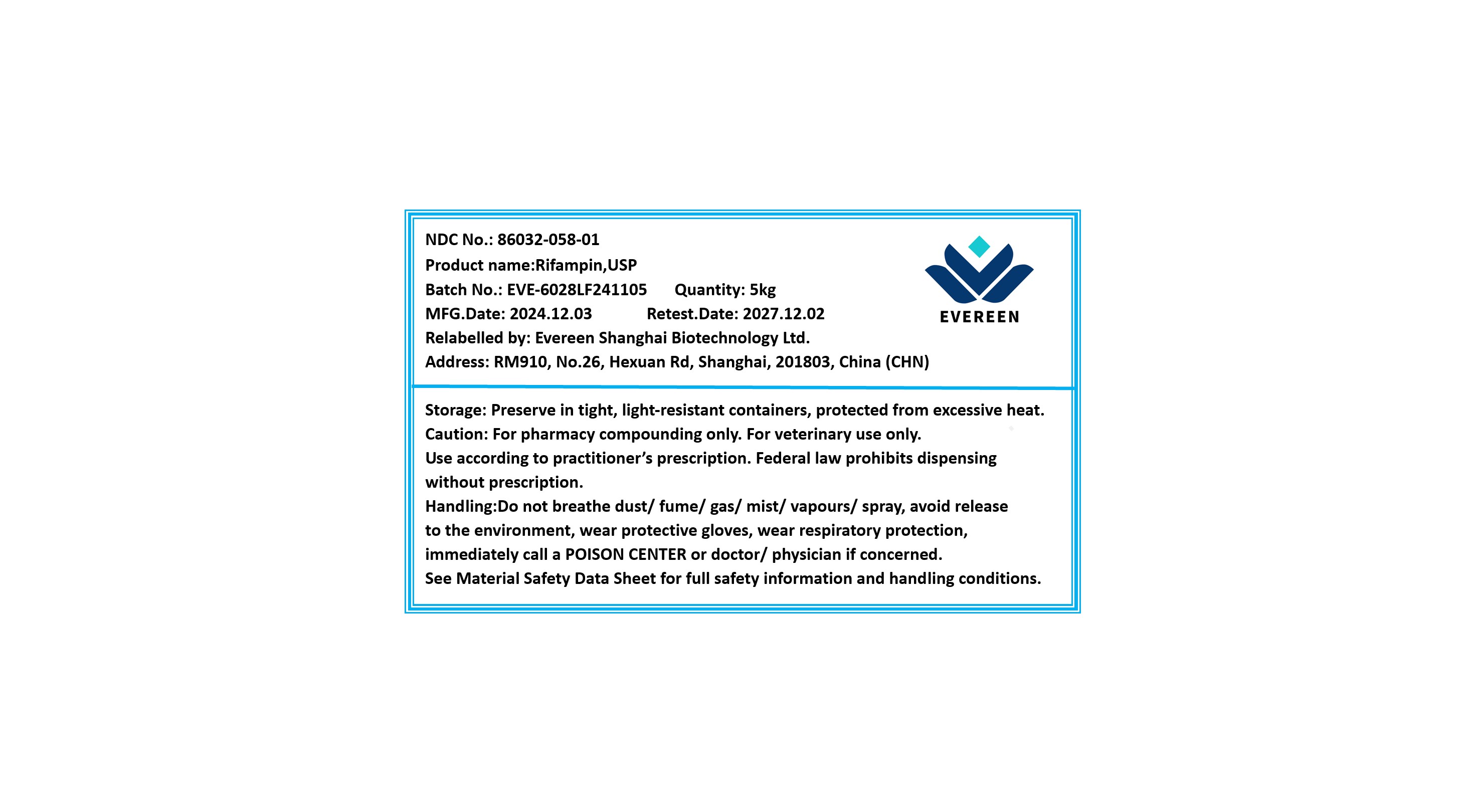 DRUG LABEL: RIFAMPIN (RIFAMPICIN)
NDC: 86032-058 | Form: POWDER
Manufacturer: Evereen Shanghai Biotechnology Ltd.
Category: other | Type: BULK INGREDIENT - ANIMAL DRUG
Date: 20250916

ACTIVE INGREDIENTS: RIFAMPIN 1 kg/1 kg

Rifampin